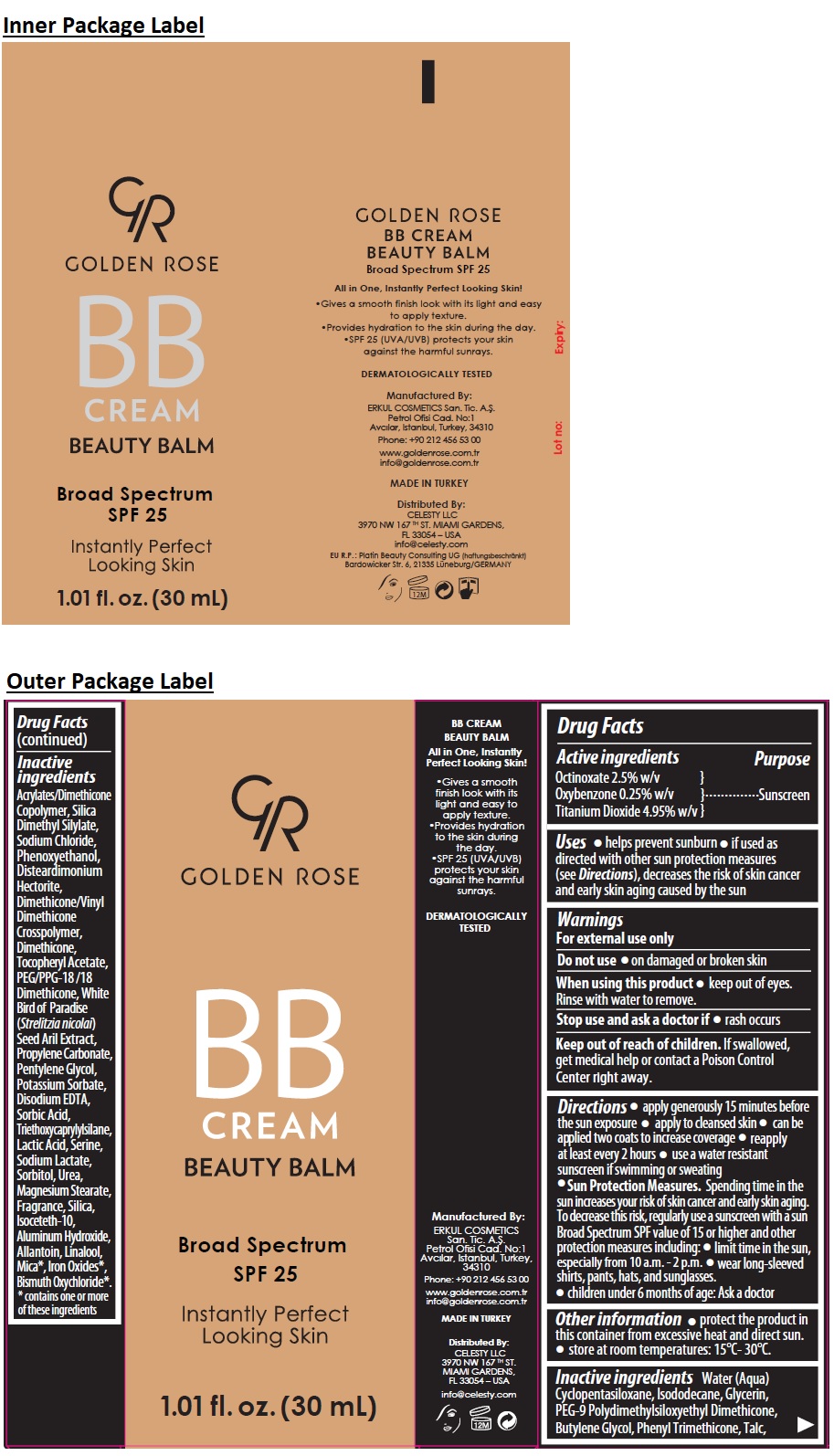 DRUG LABEL: GR BB SPF 25
NDC: 82715-101 | Form: CREAM
Manufacturer: ERKUL KOZMETIK SANAYI VE TICARET ANONIM SIRKETI
Category: otc | Type: HUMAN OTC DRUG LABEL
Date: 20250806

ACTIVE INGREDIENTS: OCTINOXATE 2.5 g/100 mL; OXYBENZONE 0.25 g/100 mL; TITANIUM DIOXIDE 4.95 g/100 mL
INACTIVE INGREDIENTS: WATER; CYCLOMETHICONE 5; ISODODECANE; GLYCERIN; PEG-9 POLYDIMETHYLSILOXYETHYL DIMETHICONE; BUTYLENE GLYCOL; PHENYL TRIMETHICONE; TALC; 2-ETHYLHEXYL ACRYLATE, METHACRYLATE, METHYL METHACRYLATE, OR BUTYL METHACRYLATE/HYDROXYPROPYL DIMETHICONE COPOLYMER (30000-300000 MW); SILICA DIMETHYL SILYLATE; SODIUM CHLORIDE; PHENOXYETHANOL; DISTEARDIMONIUM HECTORITE; DIMETHICONE/VINYL DIMETHICONE CROSSPOLYMER (SOFT PARTICLE); DIMETHICONE, UNSPECIFIED; .ALPHA.-TOCOPHEROL ACETATE; PEG/PPG-18/18 DIMETHICONE; STRELITZIA NICOLAI WHOLE; PROPYLENE CARBONATE; PENTYLENE GLYCOL; POTASSIUM SORBATE; EDETATE DISODIUM ANHYDROUS; SORBIC ACID; TRIETHOXYCAPRYLYLSILANE; LACTIC ACID, UNSPECIFIED FORM; SERINE; SODIUM LACTATE; SORBITOL; UREA; MAGNESIUM STEARATE; SILICON DIOXIDE; ISOCETETH-10; ALUMINUM HYDROXIDE; ALLANTOIN; LINALOOL, (+/-)-; MICA; FERRIC OXIDE RED; BISMUTH OXYCHLORIDE

GR GOLDEN ROSE BB CREAM BEAUTY BALM

Active ingredients

Octinoxate 2.5% w/v
Oxybenzone 0.25% w/v
Titanium Dioxide 4.95% w/v

Purpose

Sunscreen

Uses

• helps prevent sunburn • if used as directed with other sun protection measures (see Directions), decreases the risk of skin cancer and early skin aging caused by the sun

Warnings

For external use only

Do not use • on damaged or broken skin

When using this product • keep out of eyes. Rinse with water to remove.

Stop use and ask a doctor if • rash occurs

Keep out of reach of children. If swallowed, get medical help or contact a Poison Control Center right away.

Directions

• apply generously 15 minutes before the sun exposure • apply to cleansed skin • can be applied two coats to increase coverage • reapply at least every 2 hours • use a water resistant sunscreen if swimming or sweating
• Sun Protection Measures. Spending time in the sun increases your risk of skin cancer and early skin aging. To decrease this risk, regularly use a sunscreen with a sun Broad Spectrum SPF value of 15 or higher and other protection measures including: • limit time in the sun, especially from 10 a.m. - 2 p.m. • wear long-sleeved shirts, pants, hats, and sunglasses.
• children under 6 months of age: Ask a doctor

Other information

• protect the product in this container from excessive heat and direct sun. • store at room temperatures: 15°C- 30°C.

Inactive ingredients

Water (Aqua), Cyclopentasiloxane, Isododecane, Glycerin, PEG-9 Polydimethylsiloxyethyl Dimethicone, Butylene Glycol, Phenyl Trimethicone, Talc, Acrylates/Dimethicone Copolymer, Silica Dimethyl Silylate, Sodium Chloride, Phenoxyethanol, Disteardimonium Hectorite, Dimethicone/Vinyl Dimethicone Crosspolymer, Dimethicone, Tocopheryl Acetate, PEG/PPG-18 /18 Dimethicone, White Bird of Paradise (Strelitzia nicolai) Seed Aril Extract, Propylene Carbonate, Pentylene Glycol, Potassium Sorbate, Disodium EDTA, Sorbic Acid, Triethoxycaprylylsilane, Lactic Acid, Serine, Sodium Lactate, Sorbitol, Urea, Magnesium Stearate, Fragrance, Silica, Isoceteth-10, Aluminum Hydroxide, Allantoin, Linalool, Mica*, Iron Oxides*, Bismuth Oxychloride*.
* contains one or more of these ingredients

BB CREAM

BEAUTY BALM

Broad Spectrum SPF 25

All in One, Instantly Perfect Looking Skin!

• Gives a smooth finish look with its light and easy to apply texture.
• Provides hydration to the skin during the day.
• SPF 25 (UVA/UVB) protects your skin against the harmful sunrays.

DERMATOLOGICALLY TESTED

Manufactured By:

ERKUL COSMETICS
San. Tic. A.Ş.
Petrol Ofisi Cad. No:1
Avcılar, Istanbul, Turkey,
34310

Phone: +90 212 456 53 00

www.goldenrose.com.tr
info@goldenrose.com.tr

MADE IN TURKEY

Distributed By:

CELESTY LLC
3970 NW 167 TH ST.
MIAMI GARDENS,
FL 33054 – USA

info@celesty.com

EU R.P. : Platin Beauty Consulting UG (haftungsbeschränkt)
Bardowicker Str. 6, 21335 Lüneburg/GERMANY